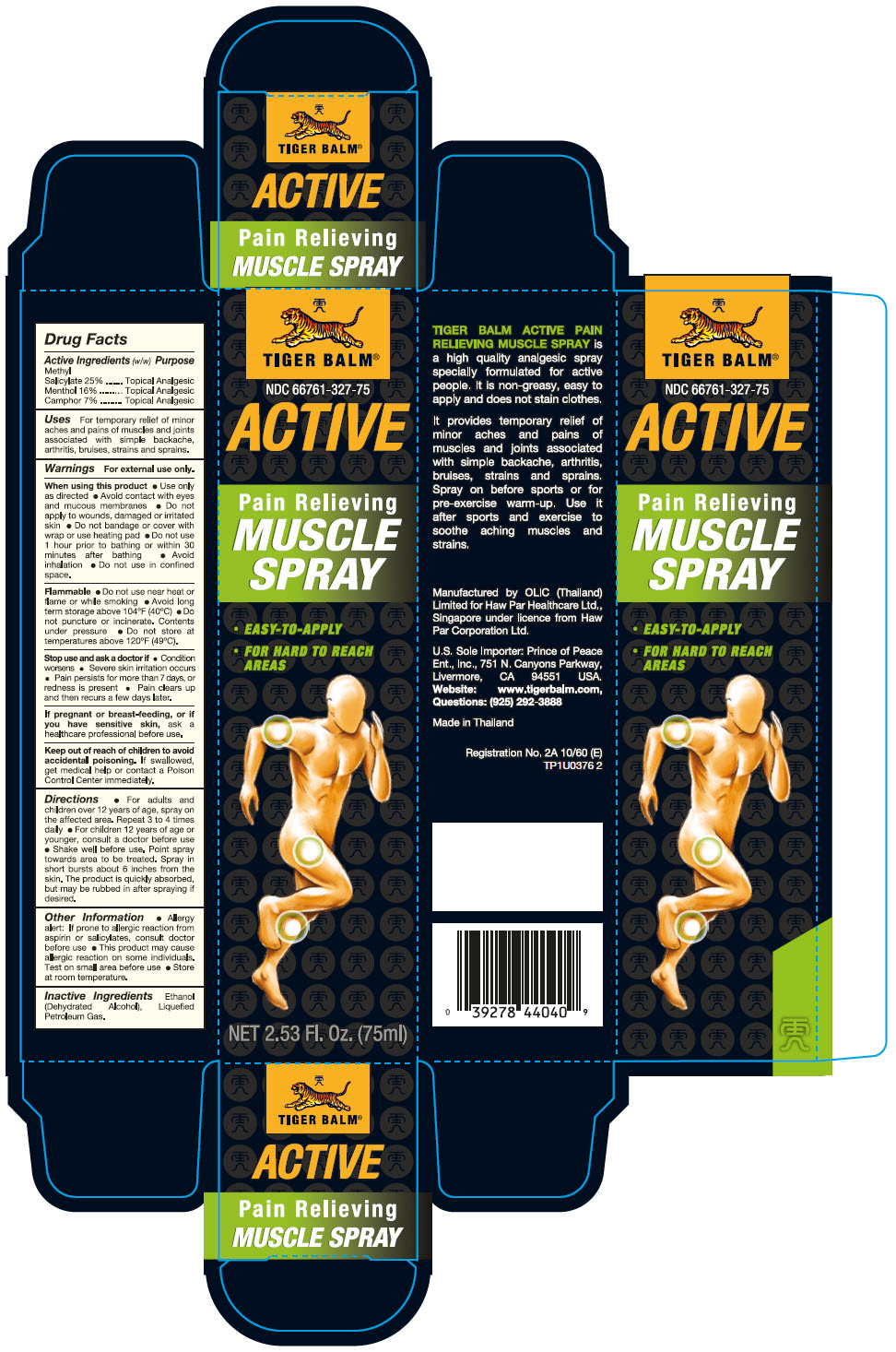 DRUG LABEL: Tiger Balm 
NDC: 66761-327 | Form: SPRAY
Manufacturer: Haw Par Healthcare Ltd.
Category: otc | Type: HUMAN OTC DRUG LABEL
Date: 20250203

ACTIVE INGREDIENTS: Methyl Salicylate 250 mg/1 mL; Menthol, Unspecified Form 160 mg/1 mL; Camphor (Synthetic) 70 mg/1 mL
INACTIVE INGREDIENTS: Alcohol; Liquefied Petroleum Gas

Tiger Balm®
Pain Relieving Muscle

Drug Facts

ACTIVE INGREDIENT

Active Ingredients (w/w) | Purpose
Methyl Salicylate 25% | Topical Analgesic
Menthol 16% | Topical Analgesic
Camphor 7% | Topical Analgesic

Uses

For temporary relief of minor aches and pains of muscles and joints associated with simple backache, arthritis, bruises, strains and sprains.

Warnings

For external use only.

When using this product

- Use only as directed
- Avoid contact with eyes and mucous membranes
- Do not apply to wounds, damaged or irritated skin
- Do not bandage or cover with wrap or use heating pad
- Do not use 1 hour prior to bathing or within 30 minutes after bathing
- Avoid inhalation
- Do not use in confined space.

Flammable

- Do not use near heat or flame or while smoking
- Avoid long term storage above 104°F (40°C)
- Do not puncture or incinerate. Contents under pressure
- Do not store at temperatures above 120°F (49°C).

Stop use and ask a doctor if

- Condition worsens
- Severe skin irritation occurs
- Pain persists for more than 7 days
- Pain clears up and then recurs a few days later.

PREGNANCY OR BREAST FEEDING

If pregnant or breast-feeding, or if you have sensitive skin, ask a healthcare professional before use.

Keep out of reach of children. If swallowed, get medical help or contact a Poison Control Center immediately.

Directions

- For adults and children over 12 years of age, spray on the affected area. Repeat 3 to 4 times daily
- For children 12 years of age or younger, consult a doctor before use
- Shake well before use. Point spray towards area to be treated. Spray in short bursts about 6 inches from the skin. The product is quickly absorbed, but may be rubbed in after spraying if desired.

Other Information

- Allergy alert: If prone to allergic reaction from aspirin or salicylates, consult doctor before use
- This product may cause allergic reaction on some individuals. Test on small area before use
- Store at room temperature.

Inactive Ingredients

Ethanol (Dehydrated Alcohol), Liquefied Petroleum Gas.

Questions

(925) 292-3888

Manufactured by OLIC (Thailand) Limited for Haw Par Healthcare Ltd., Singapore under licence from Haw Par Corporation Ltd.

PRINCIPAL DISPLAY PANEL - 75 ml Canister Carton

TIGER BALM®

NDC 66761-327-75

ACTIVE

Pain Relieving
MUSCLE
SPRAY

- EASY-TO-APPLY
- FOR HARD TO REACH
  AREAS

NET 2.53 Fl. Oz. (75ml)